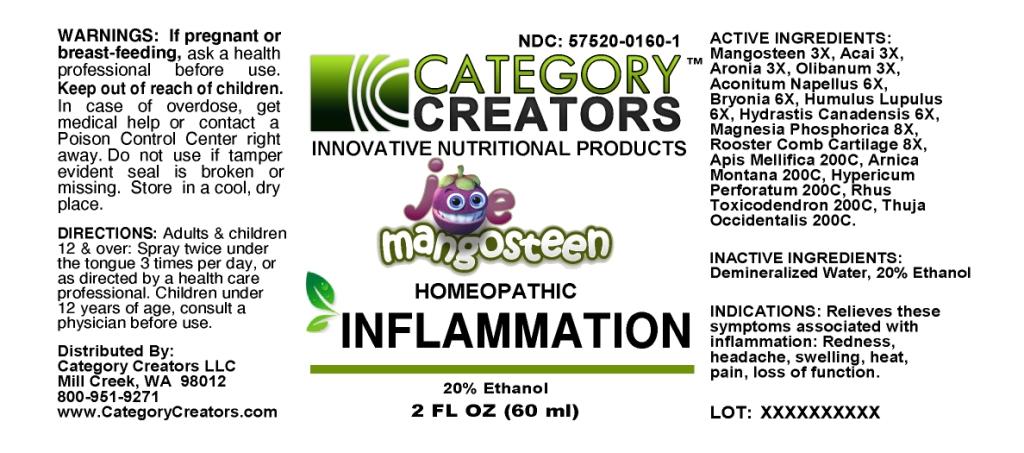 DRUG LABEL: Inflammation
NDC: 57520-0160 | Form: SPRAY
Manufacturer: Apotheca Company
Category: homeopathic | Type: HUMAN OTC DRUG LABEL
Date: 20100813

ACTIVE INGREDIENTS: ACAI 3 [hp_X]/1 mL; FRANKINCENSE 3 [hp_X]/1 mL; ACONITUM NAPELLUS 6 [hp_X]/1 mL; BRYONIA ALBA ROOT 6 [hp_X]/1 mL; HOPS 6 [hp_X]/1 mL; GOLDENSEAL 6 [hp_X]/1 mL; MAGNESIUM PHOSPHATE, DIBASIC TRIHYDRATE 8 [hp_X]/1 mL; APIS MELLIFERA 200 [hp_C]/1 mL; ARNICA MONTANA 200 [hp_C]/1 mL; HYPERICUM PERFORATUM 200 [hp_C]/1 mL; TOXICODENDRON PUBESCENS LEAF 200 [hp_C]/1 mL; THUJA OCCIDENTALIS LEAFY TWIG 200 [hp_C]/1 mL
INACTIVE INGREDIENTS: WATER; ALCOHOL

Inflammation

ACTIVE INGREDIENT

ACTIVE INGREDIENTS: Mangosteen 3X, Acai 3X, Aronia 3X, Olibanum 3X, Aconitum napellus 6X, Bryonia 6X, Humulus lupulus 6X, Hydrastis canadensis 6X, Magnesia phosphorica 8X, Rooster comb cartilage 8X, Apis mellifica 200C, Arnica montana 200C, Hypericum perforatum 200C, Rhus toxicodendron 200C, Thuja occidentalis 200C.

PURPOSE

INDICATIONS: Relieves these symptoms associated with inflammation: Redness, headache, swelling, heat, pain, loss of function.

KEEP OUT OF REACH OF CHILDREN: In case of overdose, get medical help or contact a Poison Control Center right away.

INDICATIONS AND USAGE

INDICATIONS: Relieves these symptoms associated with inflammation: Redness, headache, swelling, heat, pain, loss of function.

WARNINGS

WARNINGS: If pregnant or breast-feeding, ask a health professional before use.

Do not use if tamper evident seal is broken or missing.

Store in a cool, dry place.

DOSAGE AND ADMINISTRATION

DIRECTIONS: Adults and children 12 and over: Spray twice under the tongue 3 times per day, or as directed by a health care professional.

Children under 12 years of age, consult a physician before use.

INACTIVE INGREDIENTS: Demineralized water, 20% Ethanol.

QUESTIONS

Distributed by:

Category Creators LLC

Mill Creek, WA 98012

800-951-9271

www.CategoryCreators.com

PACKAGE LABEL

NDC: 57520-0160-1

CATEGORY CREATORS

INNOVATIVE NUTRITIONAL PRODUCTS

JOE MANGOSTEEN

HOMEOPATHIC

INFLAMMATION

2 FL OZ (60 ml)